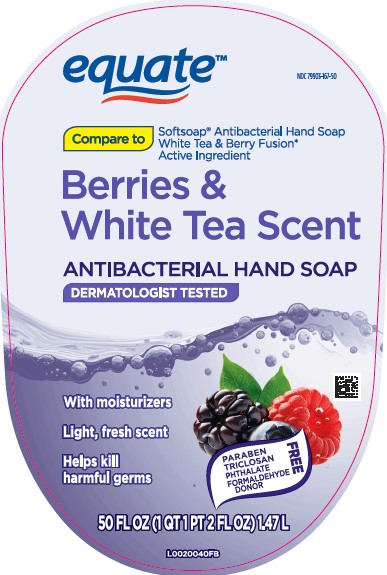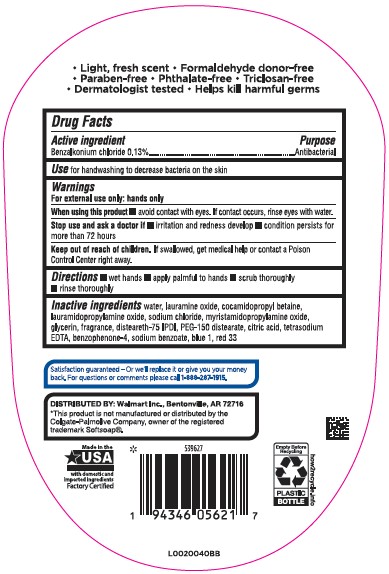 DRUG LABEL: Benzalkonium Chloride
NDC: 79903-167 | Form: GEL
Manufacturer: Walmart Inc.
Category: otc | Type: HUMAN OTC DRUG LABEL
Date: 20260227

ACTIVE INGREDIENTS: BENZALKONIUM CHLORIDE 1.3 mg/1 mL
INACTIVE INGREDIENTS: WATER; LAURAMINE OXIDE; COCAMIDOPROPYL BETAINE; LAURAMIDOPROPYLAMINE OXIDE; SODIUM CHLORIDE; MYRISTAMIDOPROPYLAMINE OXIDE; GLYCERIN; DISTEARETH-75 ISOPHORONE DIISOCYANATE; PEG-150 DISTEARATE; CITRIC ACID MONOHYDRATE; EDETATE SODIUM; SULISOBENZONE; SODIUM BENZOATE; FD&C BLUE NO. 1; D&C RED NO. 33

Equate 897.003/897AC
Antibacterial Hand Soap Berries & White Tea

Claims

- Light, fresh scent
- Formaldehyde donor-free
- Paraben-free
- Phthalate-free
- Triclosan-free
- Dermatologist tested
- Helps kill harmful germs

Active ingredient

Benzalkonium Chloride 0.13%

Purpose

Antibacterial

Use

for handwashing to decrease bacteria on the skin

Warnings

For external use only: hands only

When using this product

avoid conctact with eyes. If contact occurs, rinse eyes with water.

Stop use and ask a doctor if

- irritation and redness develop
- condition persists for more than 72 hours

Keep out of reach of children.

If swallowed, get medical help or contact a Poison Control Center rght away.

Directions

- wet hands
- apply palmful to hands
- scrub thoroughly
- rinse thoroughly

inactive ingredients

water, lauramine oxide, cocamidopropyl betaine, lauramidopropylamine oxide, sodium chloride, myristamidopropylamine oxide, glycerin, fragrance, disteareth-75 IPDI, PEG-150 distearate, citric acid, tetrasodium EDTA, benzophenone-4, sodium benzoate, blue 1, red 33

ADVERSE REACTION

Satisfaction guaranteed - Or we'll replace it or give you your money back. For questions or comments please call 1-888-287-1915.

DISTRIBUTED BY: Walmart Inc., Bentonville, AR 72716

*This product is not manufactured or distributed by the Colgate-Palmolive Company, owner of the registered trademark Softsoap®.

Made in the USA with domestic and imported ingredients

Factory Certified

how2recycle.info

Empty bottle before recycling

PLASTIC BOTTLE

principal display panel

equate™

NDC 79903-167-50

Compare to Softsoap®Antibacterial Hand Soap White Tea & Berry Fusion* active ingredient

Berries & White Tea Scent

ANTIBACTERIAL HAND SOAP

DERMATIOLOGIST TESTED

With Moisturizers

Light, fresh scent

Helps kill harmful germs

FREE:

- PARABEN
- TRICLOSAN
- PHTHALATE
- FORMALDEHYDE DONOR

50 FL OZ (1 QT 1PT 2 FL OZ) 1.47 L